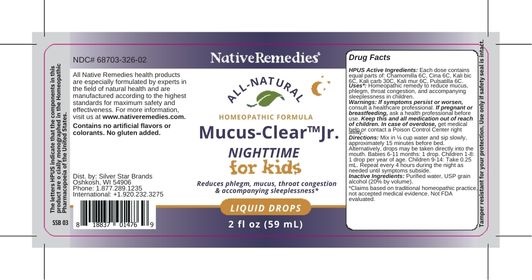 DRUG LABEL: Mucus-Clear Jr. Nighttime
NDC: 68703-326 | Form: LIQUID
Manufacturer: Silver Star Brands
Category: homeopathic | Type: HUMAN OTC DRUG LABEL
Date: 20250101

ACTIVE INGREDIENTS: ARTEMISIA CINA FLOWER 6 [hp_C]/59 mL; POTASSIUM CARBONATE 30 [hp_C]/59 mL; POTASSIUM DICHROMATE 6 [hp_C]/59 mL; POTASSIUM CHLORIDE 6 [hp_C]/59 mL; PULSATILLA VULGARIS 6 [hp_C]/59 mL; MATRICARIA RECUTITA 6 [hp_C]/59 mL
INACTIVE INGREDIENTS: ALCOHOL; WATER

NativeRemedies® Mucus-Clear™ Jr. Nighttime

HPUS Active Ingredients: Each dose contains equal parts of: Chamomilla 6C, Cina 6C, Kali bic 6C, Kali carb 30C, Kali mur 6C, Pulsatilla 6C.

The letters HPUS indicate that the components in this product are officially monographed in the Homeopathic Pharmacopoeia of the United States.

Uses*

Uses*: Homeopathic remedy to reduce mucus, phlegm, throat congestion, and accompanying sleeplessness.

*Claims based on traditional homeopathic practice, not accepted medical evidence. Not FDA evaluated.

Warnings

Warnings: I f symptoms persist or worsen, consult a healthcare professional. If pregnant or breastfeeding, ask a health professional before use. Keep this and all medication out of reach of children. In case of overdose, get medical help or contact a Poison Control Center right away.

Directions

Directions: Mix in 1/4 cup water and sip slowly, approximately 15 minutes before bed. Alternatively, drops may be taken directly into the mouth. Babies 6-11 months: 1 drop. Children 1-8: 1 drop per year of age. Children 9-14: Take 0.25 mL. Repeat every 4 hours during the night as needed until symptoms subside.

OTHER SAFETY INFORMATION

Contains no artificial flavors or colorants. No gluten added.

Tamper resistant for your protection. Use only if safety seal is intact.

Inactive Ingredients

Inactive Ingredients: Purified water, USP grain alcohol (20% by volume).

KEEP OUT OF REACH OF CHILDREN

Keep this and all medication out of reach of children.

PREGNANCY OR BREAST FEEDING

If pregnant or breastfeeding, ask a health professional before use.

PURPOSE

Temporarily relieves common cold symptoms & accompanying sleeplessness in children